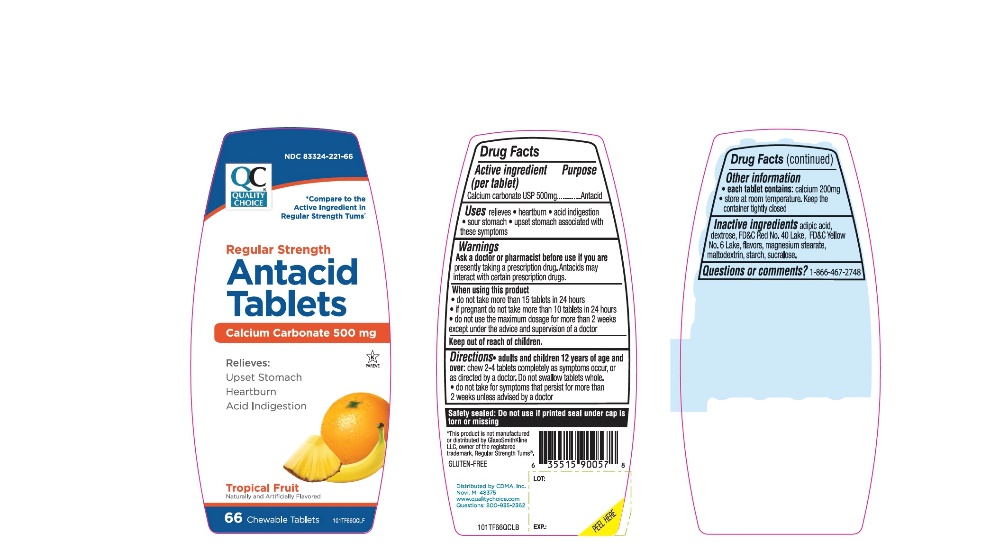 DRUG LABEL: QUALITY CHOICE
NDC: 83324-221 | Form: TABLET, CHEWABLE
Manufacturer: QUALITY CHOICE (Chain drug Marketing Assoiciation)
Category: otc | Type: HUMAN OTC DRUG LABEL
Date: 20251204

ACTIVE INGREDIENTS: CALCIUM CARBONATE 500 mg/1 1
INACTIVE INGREDIENTS: ADIPIC ACID; DEXTROSE, UNSPECIFIED FORM; FD&C RED NO. 40; FD&C YELLOW NO. 6; MAGNESIUM STEARATE; MALTODEXTRIN; STARCH, CORN; SUCRALOSE

QC Regular Strength Antacid Chewable Tablets 66 count

Active ingredient

Calcium carbonate USP 500mg

Purpose

Antacid

Uses

- relieves:
  - heartburn
  - sour stomach
  - acid indigestion
  - upset stomach associated with these symptoms

Warnings

Ask a doctor or pharmacist before use if you aretaking a prescription drug. Antacids may interact with certain prescription drugs.

When using this product

- do not take more than 15 tablets in 24 hours
- If pregnant do not take more than 10 tablets in 24 hours
- do not use the maximum dosage for more than 2 weeks except under the advice and super vision of a doctor.

Directions

- adults and children 12 years of age and over:Chew 2-4 tablets as symptoms occur, or as directed by a doctor.do not swallow tablets whole.
- Do not take for symptoms that persist for more than 2 weeks unless advised by a doctor

Other information

- each tablet contains: calcium 200mg
- Store at room temperature. Keep the container tightly closed

Inactive ingredients

adipic acid, dextrose, FD&C Red No. 40 Lake, FD & C Yellow No. 6 Lake, flavors, magnesium stearate, maltodextrin, starch, sucralose.

Questions or comments?

1-866-467-2748

Package/Label Principal Display Panel

NDC 83324-221-66

QC

*Compare to the Active Ingredient in Regular Strength Tums*

Regular Strength

Antacid Tablets

Calcium Carbonate 500 mg

- Relieves:

- Acid Indigestion
- Upset Stomach
- Heartburn

Tropical Fruit

Naturally and Artificially Flavored

66 Chewable Tablets

Distributed by:

CDMA, Inc.

Novi, MI 48375

www.qualitychoice.com

Questions: 800-35-2362

*This product is not manufactured or distributed by GlaxoSmithKline LLC, owner of the registered trademark, Regular Strength TUMS®.

Safety sealed: Do not use if printed seal under cap is torn or missing